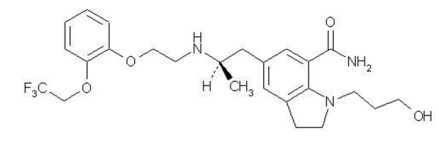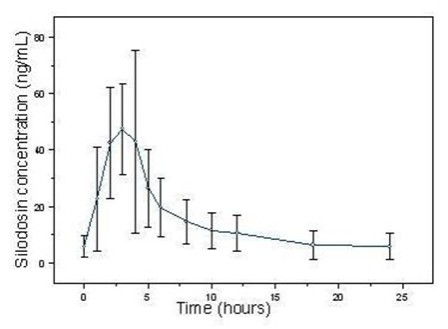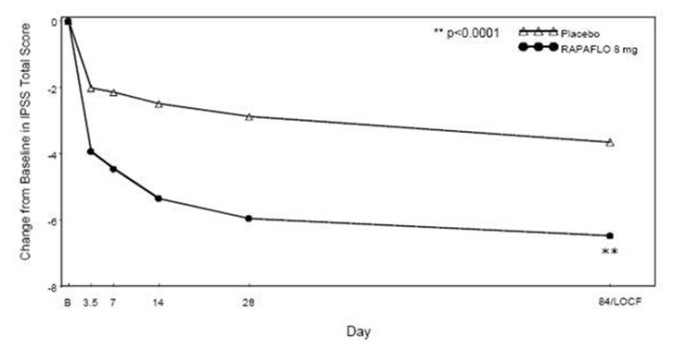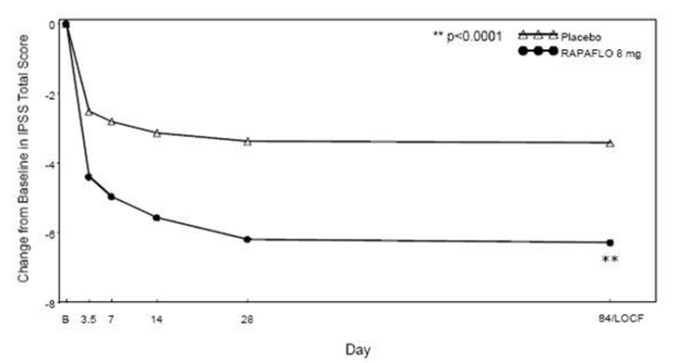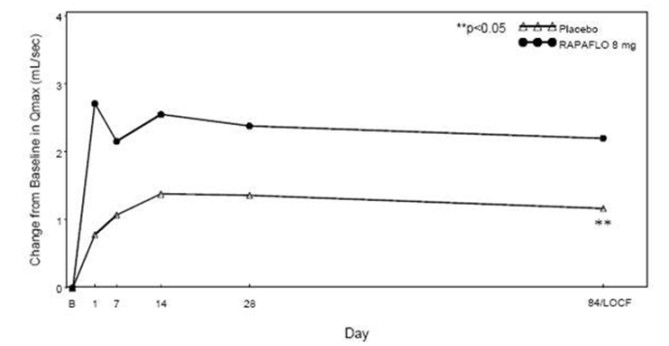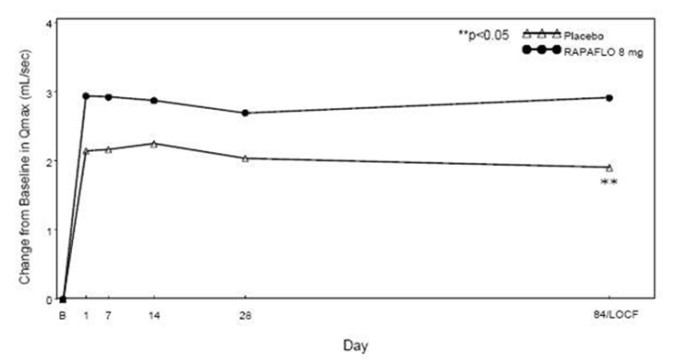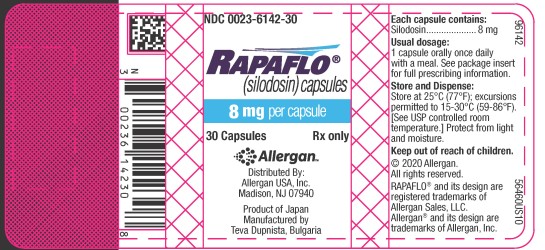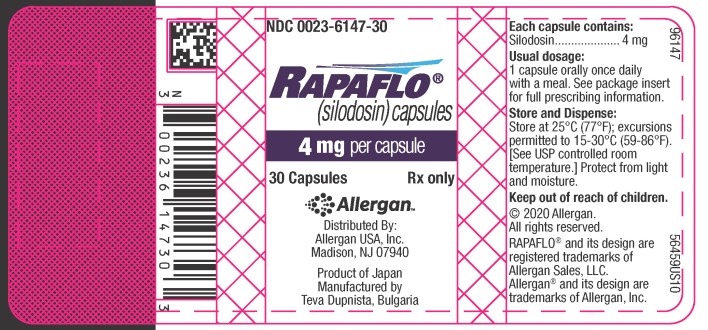 DRUG LABEL: RAPAFLO
NDC: 0023-6142 | Form: CAPSULE
Manufacturer: Allergan, Inc.
Category: prescription | Type: HUMAN PRESCRIPTION DRUG LABEL
Date: 20201201

ACTIVE INGREDIENTS: SILODOSIN 8 mg/1 1

HIGHLIGHTS OF PRESCRIBING INFORMATION

These highlights do not include all the information needed to use RAPAFLO safely and effectively. See full prescribing information for RAPAFLO.
RAPAFLO® (silodosin) capsules, for oral use
Initial U.S. Approval: 2008

1 INDICATIONS AND USAGE

RAPAFLO, an alpha-1 adrenergic receptor antagonist, is indicated for the treatment of the signs and symptoms of benign prostatic hyperplasia (BPH). RAPAFLO is not indicated for the treatment of hypertension. (1)

2 DOSAGE AND ADMINISTRATION

- 8 mg capsules taken orally once daily with a meal. (2.1)
- 4 mg capsules taken orally once daily with a meal for those with moderate renal impairment [Creatinine Clearance (CCr) 30-50 mL/min]. (2.2)

3 DOSAGE FORMS AND STRENGTHS

Capsules: 8 mg and 4 mg. (3)

4 CONTRAINDICATIONS

- Patients with severe renal impairment [Creatinine Clearance (CCr < 30 mL/min)]. (4)
- Patients with severe hepatic impairment (Child-Pugh score > 10). (4)
- Concomitant administration with strong Cytochrome P450 3A4 (CYP3A4) inhibitors (e.g., ketoconazole, clarithromycin, itraconazole, ritonavir). (4)
- Patients with a history of hypersensitivity to silodosin or any of the ingredients of RAPAFLO. (4)

5 WARNINGS AND PRECAUTIONS

- Postural hypotension, with or without symptoms (e.g., dizziness), may develop when beginning RAPAFLO treatment. (5.1)
- In patients with moderate renal impairment, RAPAFLO dose should be reduced to 4 mg once daily. (5.2)
- RAPAFLO should not be used in combination with other alpha-blockers. (5.5)
- Examine patients thought to have BPH prior to starting therapy with RAPAFLO to rule out the presence of carcinoma of the prostate. (5.6)
- Inform patients planning cataract surgery to notify their ophthalmologist that they are taking RAPAFLO because of the possibility of Intraoperative Floppy Iris Syndrome (IFIS). (5.7)

6 ADVERSE REACTIONS

Most common adverse reactions (incidence > 2%) are retrograde ejaculation, dizziness, diarrhea, orthostatic hypotension, headache, nasopharyngitis, and nasal congestion. (6)

To report SUSPECTED ADVERSE REACTIONS, contact Allergan at 1-800-678-1605 or FDA at 1-800-FDA-1088 or www.fda.gov/medwatch.

7 DRUG INTERACTIONS

- Strong P-glycoprotein inhibitors (e.g., cyclosporine): Co-administration may increase plasma silodosin concentration. Concomitant use is not recommended. (7.2)
- Alpha-blockers: Interactions involving concomitant use have not been determined. However, interactions are expected and concomitant use is not recommended. (7.3)
- Concomitant use of PDE5 inhibitors with alpha-blockers including RAPAFLO can potentially cause symptomatic hypotension. (5.5, 7.5)

8 USE IN SPECIFIC POPULATIONS

- Renal impairment: Dose adjustment in moderate disease. (2.2) Contraindicated in severe renal disease. (4)
- Hepatic impairment: Contraindicated in severe disease. (4)

FULL PRESCRIBING INFORMATION

1 INDICATIONS AND USAGE

RAPAFLO®, a selective alpha-1 adrenergic receptor antagonist, is indicated for the treatment of the signs and symptoms of benign prostatic hyperplasia (BPH) [see CLINICAL STUDIES (14)]. RAPAFLO is not indicated for the treatment of hypertension.

2 DOSAGE AND ADMINISTRATION

2.1 Dosing Information

The recommended dose is 8 mg orally once daily with a meal.

Patients who have difficulty swallowing pills and capsules may carefully open the RAPAFLO capsule and sprinkle the powder inside on a tablespoonful of applesauce. The applesauce should be swallowed immediately (within 5 minutes) without chewing and followed with an 8 oz glass of cool water to ensure complete swallowing of the powder. The applesauce used should not be hot, and it should be soft enough to be swallowed without chewing. Any powder/applesauce mixture should be used immediately (within 5 minutes) and not stored for future use. Subdividing the contents of a RAPAFLO capsule is not recommended [see CLINICAL PHARMACOLOGY (12.3)].

2.2 Dosage Adjustment in Special Populations

Renal impairment: RAPAFLO is contraindicated in patients with severe renal impairment (CCr < 30 mL/min). In patients with moderate renal impairment (CCr 30-50 mL/min), the dose should be reduced to 4 mg once daily taken with a meal. No dosage adjustment is needed in patients with mild renal impairment (CCr 50-80 mL/min) [see CONTRAINDICATIONS (4), WARNINGS AND PRECAUTIONS (5.2), USE IN SPECIFIC POPULATIONS (8.6) and CLINICAL PHARMACOLOGY (12.3)].

Hepatic impairment: RAPAFLO has not been studied in patients with severe hepatic impairment (Child-Pugh score > 10) and is therefore contraindicated in these patients. No dosage adjustment is needed in patients with mild or moderate hepatic impairment [see CONTRAINDICATIONS (4), WARNINGS AND PRECAUTIONS (5.3), USE IN SPECIFIC POPULATIONS (8.7) and CLINICAL PHARMACOLOGY (12.3)].

3 DOSAGE FORMS AND STRENGTHS

The 8 mg capsules are white, opaque, hard #1 gelatin capsules imprinted with “WATSON 152” in green on the cap and “8 mg” in green on the body.

The 4 mg capsules are white, opaque, hard #3 gelatin capsules imprinted with “WATSON 151” in gold on the cap and “4 mg” in gold on the body.

4 CONTRAINDICATIONS

- Severe renal impairment (CCr < 30 mL/min)
- Severe hepatic impairment (Child-Pugh score > 10)
- Concomitant administration with strong Cytochrome P450 3A4 (CYP3A4) inhibitors (e.g., ketoconazole, clarithromycin, itraconazole, ritonavir) [see DRUG INTERACTIONS (7.1)]
- Patients with a history of hypersensitivity to silodosin or any of the ingredients of RAPAFLO [see ADVERSE REACTIONS (6.2) and DESCRIPTION (11)]

5 WARNINGS AND PRECAUTIONS

5.1 Orthostatic Effects

Postural hypotension, with or without symptoms (e.g., dizziness) may develop when beginning RAPAFLO treatment. As with other alpha-blockers, there is potential for syncope. Patients should be cautioned about driving, operating machinery, or performing hazardous tasks when initiating therapy [see ADVERSE REACTIONS (6), USE IN SPECIFIC POPULATIONS (8.5), CLINICAL PHARMACOLOGY (12.2), and PATIENT COUNSELING INFORMATION (17)].

5.2 Renal Impairment

In a clinical pharmacology study, plasma concentrations (AUC and Cmax) of silodosin were approximately three times higher in subjects with moderate renal impairment compared with subjects with normal renal function, while half-lives of silodosin doubled in duration. The dose of RAPAFLO should be reduced to 4 mg in patients with moderate renal impairment. Exercise caution and monitor such patients for adverse events [see USE IN SPECIFIC POPULATIONS (8.6) and CLINICAL PHARMACOLOGY (12.3)].

RAPAFLO is contraindicated in patients with severe renal impairment [see CONTRAINDICATIONS (4)].

5.3 Hepatic Impairment

RAPAFLO has not been tested in patients with severe hepatic impairment, and therefore, should not be prescribed to such patients [see CONTRAINDICATIONS (4), USE IN SPECIFIC POPULATIONS (8.7) and CLINICAL PHARMACOLOGY (12.3)].

5.4 Pharmacokinetic Drug-Drug Interactions

In a drug interaction study, co-administration of a single 8 mg dose of RAPAFLO with 400 mg ketoconazole, a strong CYP3A4 inhibitor, caused a 3.8-fold increase in maximum plasma silodosin concentrations and 3.2-fold increase in silodosin exposure (i.e., AUC). Concomitant use of ketoconazole or other strong CYP3A4 inhibitors (e.g., itraconazole, clarithromycin, ritonavir) is therefore contraindicated [see DRUG INTERACTIONS (7.1)].

5.5 Pharmacodynamic Drug-Drug Interactions

The pharmacodynamic interactions between silodosin and other alpha-blockers have not been determined. However, interactions may be expected, and RAPAFLO should not be used in combination with other alpha-blockers [see DRUG INTERACTIONS (7.3)].

A specific pharmacodynamic interaction study between silodosin and antihypertensive agents has not been performed. However, patients in the Phase 3 clinical studies taking concomitant antihypertensive medications with RAPAFLO did not experience a significant increase in the incidence of syncope, dizziness, or orthostasis. Nevertheless, exercise caution during concomitant use with antihypertensives and monitor patients for possible adverse events [see ADVERSE REACTIONS (6.1) and DRUG INTERACTIONS (7.6)].

Caution is also advised when alpha-adrenergic blocking agents including RAPAFLO are co-administered with PDE5 inhibitors. Alpha-adrenergic blockers and PDE5 inhibitors are both vasodilators that can lower blood pressure. Concomitant use of these two drug classes can potentially cause symptomatic hypotension [see DRUG INTERACTIONS (7.5)].

5.6 Carcinoma of the Prostate

Carcinoma of the prostate and BPH cause many of the same symptoms. These two diseases frequently co-exist. Therefore, patients thought to have BPH should be examined prior to starting therapy with RAPAFLO to rule out the presence of carcinoma of the prostate.

5.7 Intraoperative Floppy Iris Syndrome

Intraoperative Floppy Iris Syndrome has been observed during cataract surgery in some patients on alpha-1 blockers or previously treated with alpha-1 blockers. This variant of small pupil syndrome is characterized by the combination of a flaccid iris that billows in response to intraoperative irrigation currents; progressive intraoperative miosis despite preoperative dilation with standard mydriatic drugs; and potential prolapse of the iris toward the phacoemulsification incisions. Patients planning cataract surgery should be told to inform their ophthalmologist that they are taking RAPAFLO [see ADVERSE REACTIONS (6.1)].

5.8 Laboratory Test Interactions

No laboratory test interactions were observed during clinical evaluations. Treatment with RAPAFLO for up to 52 weeks had no significant effect on prostate-specific antigen (PSA).

6 ADVERSE REACTIONS

6.1 Clinical Trials Experience

Because clinical trials are conducted under widely varying conditions, adverse reaction rates observed in the clinical trials of a drug cannot be directly compared to rates in the clinical trials of another drug and may not reflect the rates observed in clinical practice.

In U.S. clinical trials, 897 patients with BPH were exposed to 8 mg RAPAFLO daily. This includes 486 patients exposed for 6 months and 168 patients exposed for 1 year. The population was 44 to 87 years of age, and predominantly Caucasian. Of these patients, 42.8% were 65 years of age or older and 10.7% were 75 years of age or older.

In double-blind, placebo controlled, 12-week clinical trials, 466 patients were administered RAPAFLO and 457 patients were administered placebo. At least one treatment-emergent adverse reaction was reported by 55.2% of RAPAFLO treated patients (36.8% for placebo treated). The majority (72.1%) of adverse reactions for the RAPAFLO treated patients (59.8% for placebo treated) were qualified by the investigator as mild. A total of 6.4% of RAPAFLO treated patients (2.2% for placebo treated) discontinued therapy due to an adverse reaction (treatment-emergent), the most common reaction being retrograde ejaculation (2.8%) for RAPAFLO treated patients. Retrograde ejaculation is reversible upon discontinuation of treatment.

Adverse Reactions observed in at least 2% of patients:

The incidence of treatment-emergent adverse reactions listed in the following table were derived from two 12-week, multicenter, double-blind, placebo-controlled clinical studies of RAPAFLO 8 mg daily in BPH patients. Adverse reactions that occurred in at least 2% of patients treated with RAPAFLO and more frequently than with placebo are shown in Table 1.

Table 1 Adverse Reactions Occurring in ≥ 2% of Patients in 12-week, Placebo-Controlled Clinical Trials
Adverse Reactions | RAPAFLO N = 466 n (%) | Placebo N = 457 n (%)
Retrograde Ejaculation | 131 (28.1) | 4 (0.9)
Dizziness | 15 (3.2) | 5 (1.1)
Diarrhea | 12 (2.6) | 6 (1.3)
Orthostatic Hypotension | 12 (2.6) | 7 (1.5)
Headache | 11 (2.4) | 4 (0.9)
Nasopharyngitis | 11 (2.4) | 10 (2.2)
Nasal Congestion | 10 (2.1) | 1 (0.2)

In the two 12-week, placebo-controlled clinical trials, the following adverse events were reported by between 1% and 2% of patients receiving RAPAFLO and occurred more frequently than with placebo: insomnia, PSA increased, sinusitis, abdominal pain, asthenia, and rhinorrhea. One case of syncope in a patient taking prazosin concomitantly and one case of priapism were reported in the RAPAFLO treatment group.

In a 9-month open-label safety study of RAPAFLO, one case of Intraoperative Floppy Iris Syndrome (IFIS) was reported.

6.2 Postmarketing Experience

The following adverse reactions have been identified during post approval use of silodosin. Because these reactions are reported voluntarily from a population of uncertain size, it is not always possible to reliably estimate their frequency or establish a causal relationship to drug exposure:

Skin and subcutaneous tissue disorders: toxic skin eruption, purpura, skin rash, pruritus, and urticaria

Hepatobiliary disorders: jaundice, impaired hepatic function associated with increased transaminase values

Immune system disorders: allergic-type reactions, not limited to skin reactions including swollen tongue and pharyngeal edema resulting in serious outcomes

7 DRUG INTERACTIONS

7.1 Moderate and Strong CYP3A4 Inhibitors

In a clinical metabolic inhibition study, a 3.8-fold increase in silodosin maximum plasma concentrations and 3.2-fold increase in silodosin exposure were observed with concurrent administration of a strong CYP3A4 inhibitor, 400 mg ketoconazole. Use of strong CYP3A4 inhibitors such as itraconazole or ritonavir may cause plasma concentrations of silodosin to increase. Concomitant administration of strong CYP3A4 inhibitors and RAPAFLO is contraindicated [see CONTRAINDICATIONS (4), WARNINGS AND PRECAUTIONS (5.4) and CLINICAL PHARMACOLOGY (12.3)].

The effect of moderate CYP3A4 inhibitors on the pharmacokinetics of silodosin has not been evaluated. Concomitant administration with moderate CYP3A4 inhibitors (e.g., diltiazem, erythromycin, verapamil) may increase concentration of RAPAFLO. Exercise caution and monitor patients for adverse events when co-administering RAPAFLO with moderate CYP3A4 inhibitors.

7.2 Strong P-glycoprotein (P-gp) Inhibitors

In vitro studies indicated that silodosin is a P-gp substrate. Ketoconazole, a CYP3A4 inhibitor that also inhibits P-gp, caused significant increase in exposure to silodosin. Inhibition of P-gp may lead to increased silodosin concentration. RAPAFLO is therefore not recommended in patients taking strong P-gp inhibitors such as cyclosporine [see CLINICAL PHARMACOLOGY (12.3)].

7.3 Alpha-Blockers

The pharmacodynamic interactions between silodosin and other alpha-blockers have not been determined. However, interactions may be expected, and RAPAFLO should not be used in combination with other alpha-blockers [see WARNINGS AND PRECAUTIONS (5.5)].

7.4 Digoxin

The effect of co-administration of RAPAFLO and digoxin 0.25 mg/day for 7 days was evaluated in a clinical trial in 16 healthy males, aged 18 to 45 years. Concomitant administration of RAPAFLO and digoxin did not significantly alter the steady state pharmacokinetics of digoxin. No dose adjustment is required.

7.5 PDE5 Inhibitors

Co-administration of RAPAFLO with a single dose of 100 mg sildenafil or 20 mg tadalafil was evaluated in a placebo-controlled clinical study that included 24 healthy male subjects, 45 to 78 years of age. Orthostatic vital signs were monitored in the 12-hour period following concomitant dosing. During this period, the total number of positive orthostatic test results was greater in the group receiving RAPAFLO plus a PDE5 inhibitor compared with RAPAFLO alone. No events of symptomatic orthostasis or dizziness were reported in subjects receiving RAPAFLO with a PDE5 inhibitor.

7.6 Other Concomitant Drug Therapy

Antihypertensives

The pharmacodynamic interactions between silodosin and antihypertensives have not been rigorously investigated in a clinical study. However, approximately one-third of the patients in clinical studies used concomitant antihypertensive medications with RAPAFLO. The incidence of dizziness and orthostatic hypotension in these patients was higher than in the general silodosin population (4.6% versus 3.8% and 3.4% versus 3.2%, respectively). Exercise caution during concomitant use with antihypertensives and monitor patients for possible adverse events [see WARNINGS AND PRECAUTIONS (5.5)].

Metabolic Interactions

In vitro data indicate that silodosin does not have the potential to inhibit or induce cytochrome P450 enzyme systems.

7.7 Food Interactions

The effect of a moderate fat, moderate calorie meal on silodosin pharmacokinetics was variable and decreased silodosin maximum plasma concentration (Cmax) by approximately 18 to 43% and exposure (AUC) by 4 to 49% across three different studies. Safety and efficacy clinical trials for RAPAFLO were always conducted in the presence of food intake. Patients should be instructed to take silodosin with a meal to reduce risk of adverse events [see CLINICAL PHARMACOLOGY (12.3)].

8 USE IN SPECIFIC POPULATIONS

8.1 Pregnancy

Risk Summary

RAPAFLO is not indicated for use in females.

8.2 Lactation

RAPAFLO is not indicated for use in females.

8.3 Females and Males of Reproductive Potential

Infertility

Males

Possible effects on male fertility could be observed based on findings in rats at exposures that were at least two times higher than at the MRHD (based on AUC). These findings may be reversible, and the clinical relevance is unknown [see NONCLINICAL TOXICOLOGY (13.1)].

8.4 Pediatric Use

RAPAFLO is not indicated for use in pediatric patients. Safety and effectiveness in pediatric patients have not been established.

8.5 Geriatric Use

In double-blind, placebo-controlled, 12-week clinical studies of RAPAFLO, 259 (55.6%) were under 65 years of age, 207 (44.4%) patients were 65 years of age and over, while 60 (12.9%) patients were 75 years of age and over. Orthostatic hypotension was reported in 2.3% of RAPAFLO patients < 65 years of age (1.2% for placebo), 2.9% of RAPAFLO patients > 65 years of age (1.9% for placebo), and 5.0% of patients > 75 years of age (0% for placebo). There were otherwise no significant differences in safety or effectiveness between older and younger patients [see CLINICAL PHARMACOLOGY (12.3)].

8.6 Renal Impairment

The effect of renal impairment on silodosin pharmacokinetics was evaluated in a single dose study of six male patients with moderate renal impairment and seven male subjects with normal renal function. Plasma concentrations of silodosin were approximately three times higher in subjects with moderate renal impairment compared with subjects with normal renal function.

RAPAFLO should be reduced to 4 mg per day in patients with moderate renal impairment. Exercise caution and monitor patients for adverse events.

RAPAFLO has not been studied in patients with severe renal impairment. RAPAFLO is contraindicated in patients with severe renal impairment [see CONTRAINDICATIONS (4), WARNINGS AND PRECAUTIONS (5.2) and CLINICAL PHARMACOLOGY (12.3)].

8.7 Hepatic Impairment

In a study comparing nine male patients with moderate hepatic impairment (Child-Pugh scores 7 to 9), to nine healthy male subjects, the single dose pharmacokinetics of silodosin were not significantly altered in patients with hepatic impairment. No dosing adjustment is required in patients with mild or moderate hepatic impairment.

RAPAFLO has not been studied in patients with severe hepatic impairment. RAPAFLO is contraindicated in patients with severe hepatic impairment [see CONTRAINDICATIONS (4), WARNINGS AND PRECAUTIONS (5.3) and CLINICAL PHARMACOLOGY (12.3)].

10 OVERDOSAGE

RAPAFLO was evaluated at doses of up to 48 mg/day in healthy male subjects. The dose-limiting adverse event was postural hypotension.

Should overdose of RAPAFLO lead to hypotension, support of the cardiovascular system is of first importance. Restoration of blood pressure and normalization of heart rate may be accomplished by maintaining the patient in the supine position. If this measure is inadequate, administration of intravenous fluid should be considered. If necessary, vasopressors could be used, and renal function should be monitored and supported as needed. Dialysis is unlikely to be of significant benefit since silodosin is highly (97%) protein bound.

11 DESCRIPTION

RAPAFLO is the brand name for silodosin, a selective antagonist of alpha-1 adrenoreceptors. The chemical name of silodosin is 1-(3-Hydroxypropyl)-5-[(2R)-2-({2-[2-(2,2,2-trifluoroethoxy)phenoxy]ethyl}amino)propyl]-2,3-dihydro-1H-indole-7-carboxamide and the molecular formula is C25H32F3N3O4 with a molecular weight of 495.53. The structural formula of silodosin is:

Silodosin is a white to pale yellowish white powder that melts at approximately 105 to 109°C. It is very soluble in acetic acid, freely soluble in alcohol, and very slightly soluble in water.

Each RAPAFLO 8 mg capsule for oral administration contains 8 mg silodosin, and the following inactive ingredients: D-mannitol, magnesium stearate, pregelatinized starch, and sodium lauryl sulfate. The size #1 hard gelatin capsules contain gelatin and titanium dioxide. The capsules are printed with edible ink containing FD&C Blue No. 1 Aluminum Lake and yellow iron oxide.

Each RAPAFLO 4 mg capsule for oral administration contains 4 mg silodosin, and the following inactive ingredients: D-mannitol, magnesium stearate, pregelatinized starch, and sodium lauryl sulfate. The size #3 hard gelatin capsules contain gelatin and titanium dioxide. The capsules are printed with edible ink containing yellow iron oxide.

12 CLINICAL PHARMACOLOGY

12.1 Mechanism of Action

Silodosin is a selective antagonist of post-synaptic alpha-1 adrenoreceptors, which are located in the human prostate, bladder base, bladder neck, prostatic capsule, and prostatic urethra. Blockade of these alpha-1 adrenoreceptors can cause smooth muscle in these tissues to relax, resulting in an improvement in urine flow and a reduction in BPH symptoms.

An in vitro study examining binding affinity of silodosin to the three subtypes of the alpha-1 adrenoreceptors (alpha-1A, alpha-1B, and alpha-1D) was conducted. The results of the study demonstrated that silodosin binds with high affinity to the alpha-1A subtype.

12.2 Pharmacodynamics

Orthostatic Effects

A test for postural hypotension was conducted 2 to 6 hours after the first dose in the two 12-week, double-blind, placebo-controlled clinical studies. After the patient had been at rest in a supine position for 5 minutes, the patient was asked to stand. Blood pressure and heart rate were assessed at 1 minute and 3 minutes after standing. A positive result was defined as a > 30 mmHg decrease in systolic blood pressure, or a > 20 mmHg decrease in diastolic blood pressure, or a > 20 bpm increase in heart rate [see WARNINGS AND PRECAUTIONS (5.1)].

Table 2 Summary of Orthostatic Test Results in 12-week, Placebo-Controlled Clinical Trials
Time of Measurement | Test Result | RAPAFLO N = 466 n (%) | Placebo N = 457 n (%)
1 Minute After Standing | Negative | 459 (98.7) | 454 (99.6)
 | Positive | 6 (1.3) | 2 (0.4)
3 Minutes After Standing | Negative | 456 (98.1) | 454 (99.6)
 | Positive | 9 (1.9) | 2 (0.4)

Cardiac Electrophysiology

The effect of RAPAFLO on QT interval was evaluated in a double-blind, randomized, active- (moxifloxacin) and placebo-controlled, parallel-group study in 189 healthy male subjects aged 18 to 45 years. Subjects received either RAPAFLO 8 mg, RAPAFLO 24 mg, or placebo once daily for five days, or a single dose of moxifloxacin 400 mg on Day 5 only. The 24 mg dose of RAPAFLO was selected to achieve blood levels of silodosin that may be seen in a “worst-case” scenario exposure (i.e., in the setting of concomitant renal disease or use of strong CYP3A4 inhibitors) [see CONTRAINDICATIONS (4), WARNINGS AND PRECAUTIONS (5.3) and CLINICAL PHARMACOLOGY (12.3)]. QT interval was measured during a 24-hour period following dosing on Day 5 (at silodosin steady state).

RAPAFLO was not associated with an increase in individual corrected (QTcI) QT interval at any time during steady state measurement, while moxifloxacin, the active control, was associated with a maximum 9.59 msec increase in QTcI.

There has been no signal of Torsade de Pointes in the post-marketing experience with silodosin outside the United States.

12.3 Pharmacokinetics

The pharmacokinetics of silodosin have been evaluated in adult male subjects with doses ranging from 0.1 mg to 24 mg per day. The pharmacokinetics of silodosin are linear throughout this dosage range.

Absorption

The pharmacokinetic characteristics of silodosin 8 mg once daily were determined in a multi-dose, open-label, 7-day pharmacokinetic study completed in 19 healthy, target-aged (> 45 years of age) male subjects. Table 3 presents the steady state pharmacokinetics of this study.

Table 3 Mean (±SD) Steady State Pharmacokinetic Parameters in Healthy Males Following Silodosin 8 mg Once Daily with Food
Cmax (ng/mL) | tmax (hours) | t 1/2 (hours) | AUCss (ng•hr/mL)
61.6 ± 27.54 | 2.6 ± 0.90 | 13.3 ± 8.07 | 373.4 ± 164.94
Cmax = maximum concentration, tmax = time to reach Cmax, t1/2 = elimination half-life,
AUCss = steady state area under the concentration-time curve

Figure 1 Mean (±SD) Silodosin Steady State Plasma Concentration-Time Profile in Healthy Target-Aged Subjects Following Silodosin 8 mg Once Daily with Food

The absolute bioavailability is approximately 32%.

Food Effect

The maximum effect of food (i.e., co-administration with a high fat, high calorie meal) on the PK of silodosin was not evaluated. The effect of a moderate fat, moderate calorie meal was variable and decreased silodosin Cmax by approximately 18 to 43% and AUC by 4 to 49% across three different studies.

In a single-center, open-label, single-dose, randomized, two-period crossover study in twenty healthy male subjects age 21 to 43 years under fed conditions, a study was conducted to evaluate the relative bioavailability of the contents of an 8 mg capsule (size #1) of silodosin sprinkled on applesauce compared to the product administered as an intact capsule. Based on AUC0-24 and Cmax, silodosin administered by sprinkling the contents of a RAPAFLO capsule onto a tablespoonful of applesauce was found to be bioequivalent to administering the capsule whole.

Distribution

Silodosin has an apparent volume of distribution of 49.5 L and is approximately 97% protein bound.

Elimination

Metabolism

Silodosin undergoes extensive metabolism through glucuronidation, alcohol and aldehyde dehydrogenase, and cytochrome P450 3A4 (CYP3A4) pathways. The main metabolite of silodosin is a glucuronide conjugate (KMD-3213G) that is formed via direct conjugation of silodosin by UDP-glucuronosyltransferase 2B7 (UGT2B7). Co-administration with inhibitors of UGT2B7 (e.g., probenecid, valproic acid, fluconazole) may potentially increase exposure to silodosin. KMD-3213G, which has been shown in vitro to be active, has an extended half-life (approximately 24 hours) and reaches plasma exposure (AUC) approximately four times greater than that of silodosin. The second major metabolite (KMD-3293) is formed via alcohol and aldehyde dehydrogenases and reaches plasma exposures similar to that of silodosin. KMD-3293 is not expected to contribute significantly to the overall pharmacologic activity of RAPAFLO.

Excretion

Following oral administration of ^14C-labeled silodosin, the recovery of radioactivity after 10 days was approximately 33.5% in urine and 54.9% in feces. After intravenous administration, the plasma clearance of silodosin was approximately 10 L/hour.

Special Populations

Race

No clinical studies specifically investigating the effects of race have been performed.

Geriatric

In a study comparing 12 geriatric males (mean age 69 years) and 9 young males (mean age 24 years), the exposure (AUC) and elimination half-life of silodosin were approximately 15% and 20%, respectively, greater in geriatric than young subjects. No difference in the Cmax of silodosin was observed [see USE IN SPECIFIC POPULATIONS (8.5)].

Pediatric

RAPAFLO has not been evaluated in patients less than 18 years of age.

Renal Impairment

In a study with six subjects with moderate renal impairment, the total silodosin (bound and unbound) AUC, Cmax, and elimination half-life were 3.2-, 3.1-, and 2-fold higher, respectively, compared to seven subjects with normal renal function. The unbound silodosin AUC and Cmax were 2.0- and 1.5-fold higher, respectively, in subjects with moderate renal impairment compared to the normal controls.

In controlled and uncontrolled clinical studies, the incidence of orthostatic hypotension and dizziness was greater in subjects with moderate renal impairment treated with 8 mg RAPAFLO daily than in subjects with normal or mildly impaired renal function [see CONTRAINDICATIONS (4), WARNINGS AND PRECAUTIONS (5.2) and USE IN SPECIFIC POPULATIONS (8.6)].

Hepatic Impairment

In a study comparing nine male patients with moderate hepatic impairment (Child-Pugh scores 7 to 9), to nine healthy male subjects, the single dose pharmacokinetic disposition of silodosin was not significantly altered in the patients with moderate hepatic impairment. No dosing adjustment is required in patients with mild or moderate hepatic impairment. The pharmacokinetics of silodosin in patients with severe hepatic impairment have not been studied [see CONTRAINDICATIONS (4), WARNINGS AND PRECAUTIONS (5.3) and USE IN SPECIFIC POPULATIONS (8.7)].

Drug Interactions

Cytochrome P450 (CYP) 3A4 Inhibitors

Two clinical drug interaction studies were conducted in which a single oral dose of silodosin was co-administered with the strong CYP3A4 inhibitor, ketoconazole, at doses of 400 mg and 200 mg, respectively, once daily for 4 days. Co-administration of 8 mg silodosin with 400 mg ketoconazole led to 3.8-fold increase in silodosin Cmax and 3.2-fold increase in AUC. Co-administration of 4 mg silodosin with 200 mg ketoconazole led to similar increases: 3.7- and 2.9-fold in silodosin Cmax and AUC, respectively. Silodosin is contraindicated with strong CYP3A4 inhibitors.

The effect of moderate CYP3A4 inhibitors on the pharmacokinetics of silodosin has not been evaluated. Due to the potential for increased exposure to silodosin, caution should be exercised when co-administering silodosin with moderate CYP3A4 inhibitors, particularly those that also inhibit P-glycoprotein (e.g., verapamil, erythromycin).

P-glycoprotein (P-gp) Inhibitors

In vitro studies indicated that silodosin is a P-gp substrate. A drug interaction study with a strong P-gp inhibitor has not been conducted. However, in drug interaction studies with ketoconazole, a CYP3A4 inhibitor that also inhibits P-gp, significant increase in exposure to silodosin was observed [see CLINICAL PHARMACOLOGY (12.3)]. Inhibition of P-gp may lead to increased silodosin concentration. Silodosin is not recommended in patients taking strong P-gp inhibitors (e.g., cyclosporine).

Digoxin

The effect of silodosin on the pharmacokinetics of digoxin was evaluated in a multiple dose, single-sequence, crossover study of 16 healthy males, aged 18 to 45 years. A loading dose of digoxin was administered as 0.5 mg twice daily for one day. Following the loading doses, digoxin (0.25 mg once daily) was administered alone for seven days and then concomitantly with silodosin 4 mg twice a day for the next seven days. No significant differences in digoxin AUC and Cmax were observed when digoxin was administered alone or concomitantly with silodosin.

Other Metabolic Enzymes and Transporters

In vitro studies indicated that silodosin administration is not likely to inhibit the activity of CYP1A2, CYP2A6, CYP2C9, CYP2C19, CYP2D6, CYP2E1, and CYP3A4 or induce the activity of CYP1A2, CYP2C8, CYP2C9, CYP2C19, CYP3A4, and P-gp.

13 NONCLINICAL TOXICOLOGY

13.1 Carcinogenesis, Mutagenesis, and Impairment of Fertility

In a 2-year oral carcinogenicity study in rats administered doses up to 150 mg/kg/day [about 8 times the exposure at the MRHD based on AUC of silodosin], an increase in thyroid follicular cell tumor incidence was seen in male rats receiving doses of 150 mg/kg/day. Silodosin induced stimulation of thyroid stimulating hormone (TSH) secretion in the male rat as a result of increased metabolism and decreased circulating levels of thyroxine (T4). These changes are believed to produce specific morphological and functional changes in the rat thyroid including hypertrophy, hyperplasia, and neoplasia. Silodosin did not alter TSH or T4 levels in clinical trials and no effects based on thyroid examinations were noted. The relevance to human risk of these thyroid tumors in rats is not known.

In a 2-year oral carcinogenicity study in mice administered doses up to 100 mg/kg/day in males (about 9 times the exposure at the MRHD based on AUC of silodosin) and 400 mg/kg/day in females (about 72 times the exposure at the MRHD based on AUC), there were no significant tumor findings in male mice. Female mice treated for 2 years with doses of 150 mg/kg/day (about 29 times the exposure at the MRHD based on AUC) or greater had statistically significant increases in the incidence of mammary gland adenoacanthomas and adenocarcinomas. The increased incidence of mammary gland neoplasms in female mice was considered secondary to silodosin-induced hyperprolactinemia measured in the treated mice. Elevated prolactin levels were not observed in clinical trials. The relevance to human risk of prolactin-mediated endocrine tumors in mice is not known. Rats and mice do not produce glucuronidated silodosin, which is present in human serum at approximately four times the level of circulating silodosin and which has similar pharmacological activity to silodosin.

Silodosin produced no evidence of mutagenic or genotoxic potential in the in vitro Ames assay, mouse lymphoma assay, unscheduled DNA synthesis assay and the in vivo mouse micronucleus assay. A weakly positive response was obtained in two in vitro Chinese Hamster Lung (CHL) tests for chromosomal aberration assays at high, cytotoxic concentrations.

Treatment of male rats with silodosin for 15 days resulted in decreased fertility at the high dose of 20 mg/kg/day (about 2 times the exposure at the MRHD based on AUC) which was reversible following a two-week recovery period. No effect was observed at 6 mg/kg/day. The clinical relevance of this finding is not known.

In a fertility study in female rats, the high dose of 20 mg/kg/day (about 1 to 4 times the exposure at the MRHD based on AUC) resulted in estrus cycle changes, but no effect on fertility. No effect on the estrus cycle was observed at 6 mg/kg/day.

In a male rat fertility study, sperm viability and count were significantly lower after administration of 600 mg/kg/day (about 65 times the exposure at the MRHD based on AUC) for one month. Histopathological examination of infertile males revealed changes in the testes and epididymides at 200 mg/kg/day (about 30 times the exposure at the MRHD based on AUC).

14 CLINICAL STUDIES

14.1 Benign Prostatic Hyperplasia

Two 12-week, randomized, double-blind, placebo-controlled, multicenter studies were conducted with 8 mg daily of silodosin. In these two studies, 923 patients [mean age 64.6 years; Caucasian (89.3%), Hispanic (4.9%), Black (3.9%), Asian (1.2%), Other (0.8%)] were randomized and 466 patients received RAPAFLO 8 mg daily. The two studies were identical in design except for the inclusion of pharmacokinetic sampling in Study 1. The primary efficacy assessment was the International Prostate Symptom Score (IPSS) which evaluated irritative (frequency, urgency, and nocturia), and obstructive (hesitancy, incomplete emptying, intermittency, and weak stream) symptoms. Maximum urine flow rate (Qmax) was a secondary efficacy measure.

Mean changes from baseline to last assessment (Week 12) in total IPSS score were statistically significantly greater for groups treated with RAPAFLO than those treated with placebo in both studies (Table 4 and Figures 2 and 3).

Table 4 Mean Change (SD) from Baseline to Week 12 in International Prostate Symptom Score in Two Randomized, Controlled, Double-Blind Studies
 | Study 1 |  |  | Study 2
Total Symptom Score | RAPAFLO 8 mg (n = 233) | Placebo (n = 228) | p-value | RAPAFLO 8 mg (n = 233) | Placebo (n = 229) | p-value
Baseline | 21.5 (5.38) | 21.4 (4.91) |  | 21.2 (4.88) | 21.2 (4.92)
Week 12 / LOCF Change from Baseline | -6.5 (6.73) | -3.6 (5.85) | < 0.0001 | -6.3 (6.54) | -3.4 (5.83) | < 0.0001
LOCF – Last observation carried forward for those not completing 12 weeks of treatment.

Figure 2 Mean Change from Baseline in IPSS Total Score by Treatment Group
and Visit in Study 1

B - Baseline determination taken Day 1 of the study before the initial dose. Subsequent values are observed cases except for LOCF values.
LOCF - Last observation carried forward for those not completing 12 weeks of treatment.

Figure 3 Mean Change from Baseline in IPSS Total Score by Treatment Group
and Visit in Study 2

B - Baseline determination taken Day 1 of the study before the initial dose. Subsequent values are observed cases except for LOCF values.
LOCF - Last observation carried forward for those not completing 12 weeks of treatment.

Mean IPSS total score for RAPAFLO once daily groups showed a decrease starting at the first scheduled observation and remained decreased through the 12 weeks of treatment in both studies.

RAPAFLO produced statistically significant increases in maximum urinary flow rates from baseline to last assessment (Week 12) versus placebo in both studies (Table 5 and Figures 4 and 5). Mean peak flow rate increased starting at the first scheduled observation at Day 1 and remained greater than the baseline flow rate through the 12 weeks of treatment for both studies.

Table 5 Mean Change (SD) from Baseline in Maximum Urinary Flow Rate (mL/sec) in Two Randomized, Controlled, Double-Blind Studies
 | Study 1 |  |  | Study 2
Mean Maximum Flow Rate (mL/sec) | RAPAFLO 8 mg (n = 233) | Placebo (n = 228) | p-value | RAPAFLO 8 mg (n = 233) | Placebo (n = 229) | p-value
Baseline | 9.0 (2.60) | 9.0 (2.85) |  | 8.4 (2.48) | 8.7 (2.67)
Week 12 / LOCF Change from Baseline | 2.2 (4.31) | 1.2 (3.81) | 0.0060 | 2.9 (4.53) | 1.9 (4.82) | 0.0431
LOCF – Last observation carried forward for those not completing 12 weeks of treatment.

Figure 4 Mean Change from Baseline in Qmax (mL/sec) by Treatment Group and Visit in Study 1

B - Baseline determination taken Day 1 of the study before the initial dose. Subsequent values are observed cases except for LOCF values.
LOCF - Last observation carried forward for those not completing 12 weeks of treatment.
Note - The first Qmax assessments at Day 1 were taken 2 to 6 hours after patients received the first dose of double-blind medication.
Note - Measurements at each visit were scheduled 2 to 6 hours after dosing (approximate peak plasma silodosin concentration).

Figure 5 Mean Change from Baseline in Qmax (mL/sec) by Treatment Group and Visit in Study 2

B - Baseline determination taken Day 1 of the study before the initial dose. Subsequent values are observed cases except for LOCF values.

LOCF - Last observation carried forward for those not completing 12 weeks of treatment.
Note - The first Qmax assessments at Day 1 were taken 2 to 6 hours after patients received the first dose of double-blind medication.

Note - Measurements at each visit were scheduled 2 to 6 hours after dosing (approximate peak plasma silodosin concentration).

16 HOW SUPPLIED/STORAGE AND HANDLING

White, opaque, hard gelatin 8 mg capsules. Cap is imprinted with “WATSON 152” in green. Body is imprinted with “8 mg” in green. 8 mg capsules are supplied in unit of use HDPE bottles of:

- 30 capsules (NDC 0023-6142-30)
- 90 capsules (NDC 0023-6142-90)

Bottles of 30 and 90 capsules are supplied with child-resistant closures.

White, opaque, hard gelatin 4 mg capsules. Cap is imprinted with “WATSON 151” in gold. Body is imprinted with “4 mg” in gold. 4 mg capsules are supplied in unit of use HDPE bottles of:

- 30 capsules (NDC 0023-6147-30)

Bottles of 30 capsules are supplied with child-resistant closures.

Storage

Store at 25°C (77°F); excursions permitted to 15-30°C (59-86°F). [See USP controlled room temperature.] Protect from light and moisture.

Keep out of reach of children.

17 PATIENT COUNSELING INFORMATION

Advise patients to take RAPAFLO once daily with a meal [see Dosage and Administration (2.1)].

Advise patients about the possible occurrence of symptoms related to postural hypotension (such as dizziness), and should be cautioned about driving, operating machinery, or performing hazardous tasks until they know how RAPAFLO will affect them. This is especially important for those with low blood pressure or who are taking antihypertensive medications [see Warnings and Precautions (5.1)].

Counsel patients on that the most common side effect seen with RAPAFLO is an orgasm with reduced or no semen. This side effect does not pose a safety concern and is reversible with discontinuation of the product [see Adverse Reactions (6.1)].

Counsel patients to tell their ophthalmologist about the use of RAPAFLO before cataract surgery or other procedures involving the eyes, even if the patient is no longer taking RAPAFLO [see Warnings and Precautions (5.7)].
Rx only

For all medical inquiries contact:
Allergan
1-800-678-1605

Distributed by:
Allergan USA, Inc.
Madison, NJ 07940

Under license from:
Kissei Pharmaceutical Co., Ltd.
Nagano, Japan

Product of Japan
Manufactured by
Teva Dupnista, Bulgaria

© 2020 Allergan. All rights reserved.
RAPAFLO® and its design are registered trademarks of Allergan Sales, LLC.
Allergan® and its design are trademarks of Allergan, Inc.

For additional information see:
www.rapaflo.com
or call 1-866-RAPAFLO (727-2356)

v1.0USPI6142

PACKAGE LABEL

Principal Display Panel
NDC 0023-6142-30
RAPAFLO
8 mg per capsule
30 Capsules
Rx Only

PACKAGE LABEL

Principal Display Panel
NDC 0023-6147-30
RAPAFLO
4 mg per capsule
30 Capsules
Rx Only